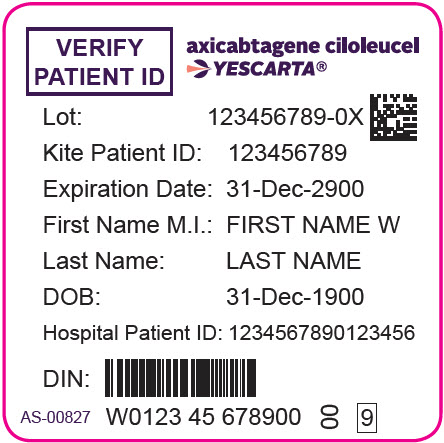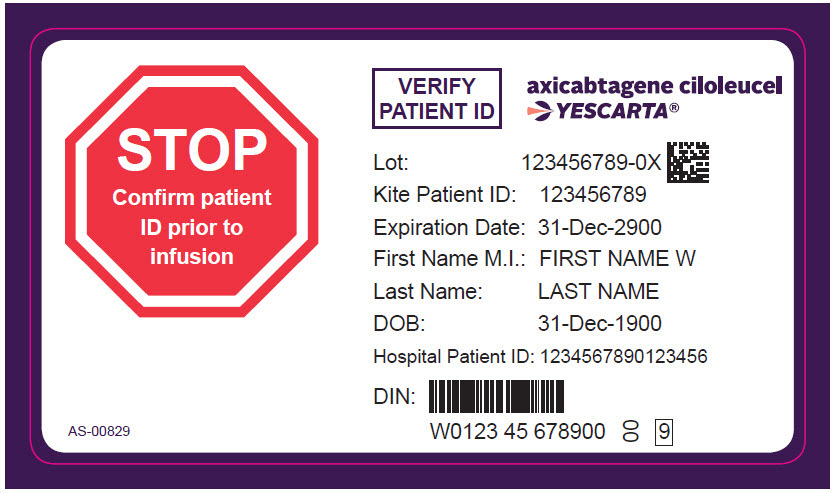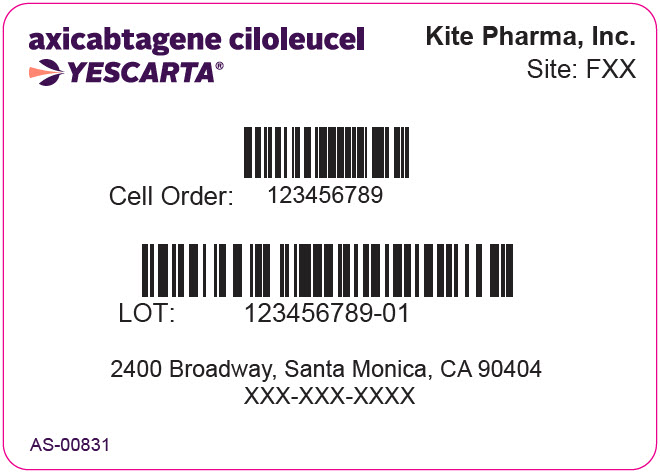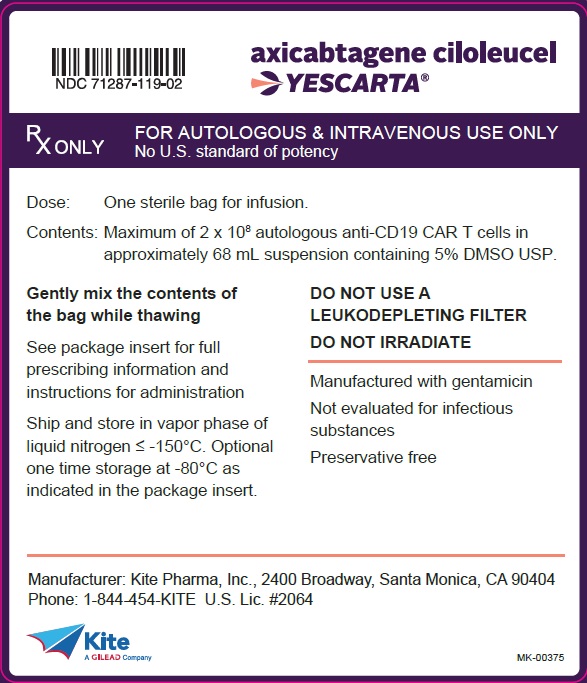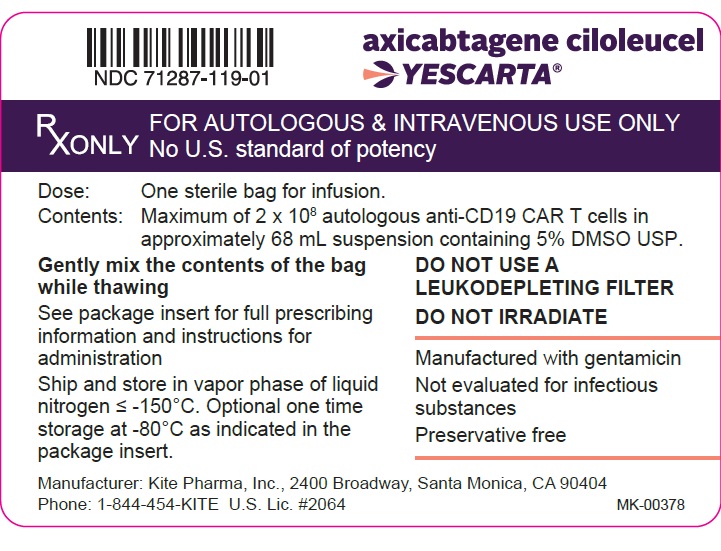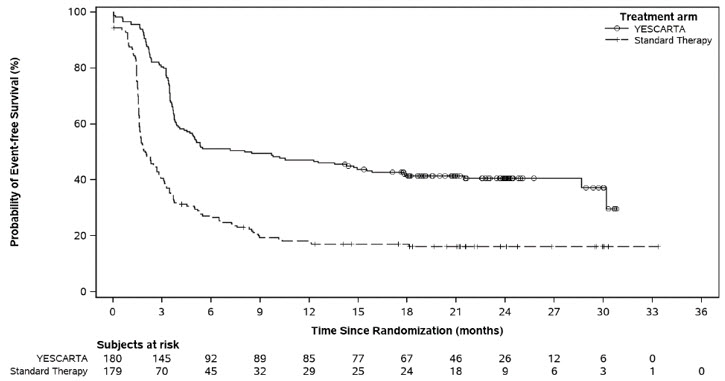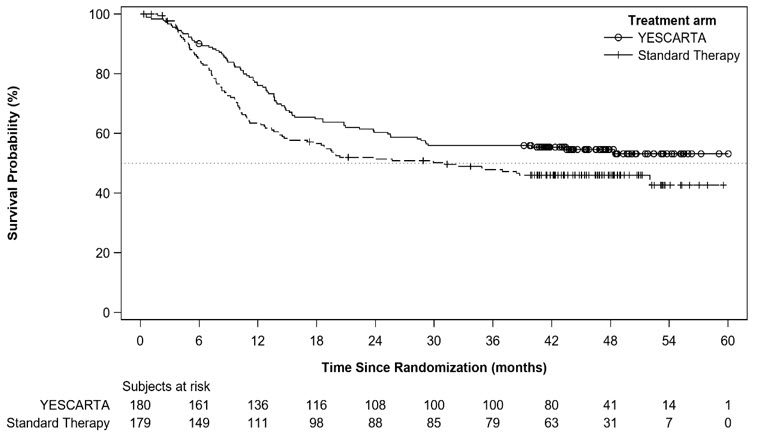 DRUG LABEL: YESCARTA
NDC: 71287-119 | Form: SUSPENSION
Manufacturer: Kite Pharma, Inc.
Category: other | Type: CELLULAR THERAPY
Date: 20260212

ACTIVE INGREDIENTS: AXICABTAGENE CILOLEUCEL 2000000 1/68 mL
INACTIVE INGREDIENTS: DIMETHYL SULFOXIDE; ALBUMIN HUMAN

HIGHLIGHTS OF PRESCRIBING INFORMATION

These highlights do not include all the information needed to use YESCARTA safely and effectively. See full prescribing information for YESCARTA.
YESCARTA® (axicabtagene ciloleucel) suspension for intravenous infusion
Initial U.S. Approval: 2017

WARNING: CYTOKINE RELEASE SYNDROME, NEUROLOGIC TOXICITIES and SECONDARY HEMATOLOGICAL MALIGNANCIES

See full prescribing information for complete boxed warning.

- Cytokine Release Syndrome (CRS), including fatal or life-threatening reactions, occurred in patients receiving YESCARTA. Do not administer YESCARTA to patients with active infection or inflammatory disorders. Treat severe or life-threatening CRS with tocilizumab or tocilizumab and corticosteroids (2.2, 2.3, 5.1).
- Neurologic toxicities, including fatal or life-threatening reactions, occurred in patients receiving YESCARTA, including concurrently with CRS or after CRS resolution. Monitor for neurologic toxicities after treatment with YESCARTA. Provide supportive care and/or corticosteroids, as needed (2.2, 2.3, 5.2).
- T cell malignancies have occurred following treatment of hematologic malignancies with BCMA- and CD19-directed genetically modified autologous T cell immunotherapies, including YESCARTA (5.7).

RECENT MAJOR CHANGES

Indications and Usage (1.1) | 02/2026
Dosage and Administration (2.2, 2.3) | 06/2025
Warnings and Precautions (5.1) | 06/2025
Warnings and Precautions (5.2) | 02/2026
Warnings and Precautions, REMS (5.3) | Removed 06/2025

1 INDICATIONS AND USAGE

YESCARTA is a CD19-directed genetically modified autologous T cell immunotherapy indicated for the treatment of:

- Adult patients with large B-cell lymphoma that is refractory to first-line chemoimmunotherapy or that relapses within 12 months of first-line chemoimmunotherapy. (1.1)
- Adult patients with relapsed or refractory large B-cell lymphoma after two or more lines of systemic therapy, including diffuse large B-cell lymphoma (DLBCL) not otherwise specified, primary mediastinal large B-cell lymphoma, high grade B-cell lymphoma, and DLBCL arising from follicular lymphoma. (1.1)
- Adult patients with relapsed or refractory follicular lymphoma (FL) after two or more lines of systemic therapy. This indication is approved under accelerated approval based on response rate. Continued approval for this indication may be contingent upon verification and description of clinical benefit in confirmatory trial(s). (1.2)

2 DOSAGE AND ADMINISTRATION

For autologous use only. For intravenous use only.

- Do NOT use a leukodepleting filter. (2.2)
- Administer a lymphodepleting regimen of cyclophosphamide and fludarabine before infusion of YESCARTA. (2.2)
- Verify the patient's identity prior to infusion. (2.2)
- Premedicate with acetaminophen and an H1-antihistamine. (2.2)
- Confirm availability of tocilizumab prior to infusion. (2.2, 5.1)
- Dosing of YESCARTA is based on the number of chimeric antigen receptor (CAR)-positive viable T cells. (2.1)
- The target YESCARTA dose is 2 × 10^6 CAR-positive viable T cells per kg body weight, with a maximum of 2 × 10^8 CAR-positive viable T cells. (2.1)

3 DOSAGE FORMS AND STRENGTHS

- YESCARTA is available as a cell suspension for infusion. (3)
- YESCARTA comprises a suspension of 2 × 10^6 CAR-positive viable T cells per kg of body weight, with a maximum of 2 × 10^8 CAR-positive viable T cells in approximately 68 mL. (3)

4 CONTRAINDICATIONS

- None. (4)

5 WARNINGS AND PRECAUTIONS

- Hypersensitivity Reactions: Monitor for hypersensitivity reactions during infusion. (5.3)
- Serious Infections: Monitor patients for signs and symptoms of infection; treat appropriately. (5.4)
- Prolonged Cytopenias: Patients may exhibit Grade 3 or higher cytopenias for several weeks following YESCARTA infusion. Monitor complete blood counts. (5.5)
- Hypogammaglobulinemia: Monitor and provide replacement therapy. (5.6)
- Secondary Malignancies: T cell malignancies have occurred following treatment of hematologic malignancies with BCMA- and CD19-directed genetically modified autologous T cell immunotherapies, including YESCARTA (5.7). In the event that a secondary malignancy occurs after treatment with YESCARTA, contact Kite at 1-844-454-KITE (5483). (5.7)

6 ADVERSE REACTIONS

The most common adverse reactions (incidence ≥ 30%), excluding laboratory abnormalities, in patients with non-Hodgkin lymphoma are CRS, fever, hypotension, encephalopathy, fatigue, tachycardia, headache, nausea, febrile neutropenia, diarrhea, musculoskeletal pain, infections with pathogen unspecified, chills and decreased appetite. (6.1)

The most common Grade 3-4 laboratory abnormalities (≥ 30%) are leukopenia, lymphopenia, neutropenia, anemia, thrombocytopenia, and hypophosphatemia. (6.1)

To report SUSPECTED ADVERSE REACTIONS, contact Kite at 1-844-454-KITE (5483) or FDA at 1-800-FDA-1088 or www.fda.gov/medwatch.

FULL PRESCRIBING INFORMATION

WARNING: CYTOKINE RELEASE SYNDROME, NEUROLOGIC TOXICITIES and SECONDARY HEMATOLOGICAL MALIGNANCIES

- Cytokine Release Syndrome (CRS), including fatal or life-threatening reactions, occurred in patients receiving YESCARTA. Do not administer YESCARTA to patients with active infection or inflammatory disorders. Treat severe or life-threatening CRS with tocilizumab or tocilizumab and corticosteroids [see Dosage and Administration (2.2, 2.3), Warnings and Precautions (5.1)].
- Neurologic toxicities, including fatal or life-threatening reactions, occurred in patients receiving YESCARTA, including concurrently with CRS or after CRS resolution. Monitor for neurologic toxicities after treatment with YESCARTA. Provide supportive care and/or corticosteroids as needed [see Dosage and Administration (2.2, 2.3), Warnings and Precautions (5.2)].
- T cell malignancies have occurred following treatment of hematologic malignancies with BCMA- and CD19-directed genetically modified autologous T cell immunotherapies, including YESCARTA [see Warnings and Precautions (5.7)].

1 INDICATIONS AND USAGE

1.1 Large B-cell Lymphoma

YESCARTA is indicated for the treatment of:

- Adult patients with large B-cell lymphoma that is refractory to first-line chemoimmunotherapy or that relapses within 12 months of first-line chemoimmunotherapy.
- Adult patients with relapsed or refractory large B-cell lymphoma after two or more lines of systemic therapy, including diffuse large B-cell lymphoma (DLBCL) not otherwise specified, primary mediastinal large B-cell lymphoma, high grade B-cell lymphoma, and DLBCL arising from follicular lymphoma.

1.2 Follicular Lymphoma

YESCARTA is indicated for the treatment of adult patients with relapsed or refractory follicular lymphoma (FL) after two or more lines of systemic therapy.

This indication is approved under accelerated approval based on response rate [see Clinical Studies (14.2)]. Continued approval for this indication may be contingent upon verification and description of clinical benefit in confirmatory trial(s).

2 DOSAGE AND ADMINISTRATION

2.1 Dose

For autologous use only. For intravenous use only.

Each single infusion bag of YESCARTA contains a suspension of chimeric antigen receptor (CAR)-positive T cells in approximately 68 mL. The target dose is 2 × 10^6 CAR-positive viable T cells per kg body weight, with a maximum of 2 × 10^8 CAR-positive viable T cells.

2.2 Administration

YESCARTA is for autologous use only. The patient's identity must match the patient identifiers on the YESCARTA cassette and infusion bag. Do not infuse YESCARTA if the information on the patient-specific label does not match the intended patient.

Preparing Patient for YESCARTA Infusion

Confirm availability of YESCARTA prior to starting the lymphodepleting regimen.

Pre-treatment

- Administer a lymphodepleting chemotherapy regimen of cyclophosphamide 500 mg/m^2 intravenously and fludarabine 30 mg/m^2 intravenously on the fifth, fourth, and third day before infusion of YESCARTA.

Premedication

- Administer acetaminophen 650 mg PO and diphenhydramine 12.5 mg intravenously or PO approximately 1 hour before YESCARTA infusion.
- Consider the use of prophylactic corticosteroid in patients after weighing the potential benefits and risks [see Warnings and Precautions (5.1 and 5.2)].

Preparation of YESCARTA for Infusion

Coordinate the timing of YESCARTA thaw and infusion. Confirm the infusion time in advance, and adjust the start time of YESCARTA thaw such that it will be available for infusion when the patient is ready.

- Confirm patient identity: Prior to YESCARTA preparation, match the patient's identity with the patient identifiers on the YESCARTA cassette.
- Do not remove the YESCARTA product bag from the cassette if the information on the patient-specific label does not match the intended patient.
- Once patient identification is confirmed, remove the YESCARTA product bag from the cassette and check that the patient information on the cassette label matches the bag label.
- Inspect the product bag for any breaches of container integrity such as breaks or cracks before thawing. If the bag is compromised, follow the local guidelines (or call Kite at 1-844-454-KITE).
- Place the infusion bag inside a second sterile bag per local guidelines.
- Thaw YESCARTA at approximately 37°C using either a water bath or dry thaw method until there is no visible ice in the infusion bag. Gently mix the contents of the bag to disperse clumps of cellular material. If visible cell clumps remain continue to gently mix the contents of the bag. Small clumps of cellular material should disperse with gentle manual mixing. Do not wash, spin down, and/or re-suspend YESCARTA in new medium prior to infusion.
- Once thawed, YESCARTA may be stored at room temperature (20°C to 25°C) for up to 3 hours.

Administration

- For autologous use only.
- Confirm that tocilizumab and emergency equipment are available prior to infusion and during the recovery period.
- Do NOT use a leukodepleting filter.
- Central venous access is recommended for the infusion of YESCARTA.
- Confirm the patient's identity matches the patient identifiers on the YESCARTA product bag.
- Prime the tubing with normal saline prior to infusion.
- Infuse the entire contents of the YESCARTA bag within 30 minutes by either gravity or a peristaltic pump. YESCARTA is stable at room temperature for up to 3 hours after thaw.
- Gently agitate the product bag during YESCARTA infusion to prevent cell clumping.
- After the entire content of the product bag is infused, rinse the tubing with normal saline at the same infusion rate to ensure all product is delivered.

YESCARTA contains human blood cells that are genetically modified with replication incompetent retroviral vector. Follow universal precautions and local biosafety guidelines for handling and disposal to avoid potential transmission of infectious diseases.

Monitoring

- Monitor patients at least daily for 7 days following infusion for signs and symptoms of CRS and neurologic toxicities.
- Instruct patients to remain within proximity of a healthcare facility for at least 2 weeks following infusion.
- Advise patients to avoid driving for at least 2 weeks following infusion.

2.3 Management of Severe Adverse Reactions

Cytokine Release Syndrome (CRS)

Identify CRS based on clinical presentation [see Warnings and Precautions (5.1)]. Evaluate for and treat other causes of fever, hypoxia, and hypotension. If CRS is suspected, manage according to the recommendations in Table 1. Patients who experience Grade 2 or higher CRS (e.g., hypotension not responsive to fluids, or hypoxia requiring supplemental oxygenation) should be monitored with continuous cardiac telemetry and pulse oximetry. For patients experiencing severe CRS, consider performing an echocardiogram to assess cardiac function. For severe or life-threatening CRS, consider intensive-care supportive therapy. Physicians may also consider management per current practice guidelines.

Table 1. CRS Grading and Management Guidance
CRS Grade [Lee et al. 2014.] | Tocilizumab | Corticosteroids
Grade 1 Symptoms require symptomatic treatment only (e.g., fever, nausea, fatigue, headache, myalgia, malaise). | If symptoms (e.g., fever) not improving after 24 hours, consider managing as Grade 2. | If not improving after 3 days, administer one dose of dexamethasone 10 mg intravenously.
Grade 2 Symptoms require and respond to moderate intervention. Oxygen requirement less than 40% FiO2 or hypotension responsive to fluids or low-dose of one vasopressor or Grade 2 organ toxicity. [Refer to Table 2 for management of neurologic toxicity.] | Administer tocilizumab [Refer to tocilizumab Prescribing Information for details.] 8 mg/kg intravenously over 1 hour (not to exceed 800 mg). If no clinical improvement in the signs and symptoms of CRS after the first dose, repeat tocilizumab every 8 hours as needed. Limit to a maximum of 3 doses in a 24-hour period; maximum total of 4 doses. If improving, discontinue tocilizumab. | Administer dexamethasone 10 mg intravenously once daily. If improving, manage as Grade 1 above and continue corticosteroids until the severity is Grade 1 or less, then quickly taper as clinically appropriate. If not improving, manage as appropriate grade below.
Grade 3 Symptoms require and respond to aggressive intervention. Oxygen requirement greater than or equal to 40% FiO2 or hypotension requiring high-dose or multiple vasopressors or Grade 3 organ toxicity or Grade 4 transaminitis. | Per Grade 2. If improving, manage as appropriate grade above. | Dexamethasone 10 mg intravenously three times a day. If improving, manage as appropriate grade above and continue corticosteroids until the severity is Grade 1 or less, then quickly taper as clinically appropriate. If not improving, manage as Grade 4.
Grade 4 Life-threatening symptoms. Requirements for ventilator support, continuous veno-venous hemodialysis (CVVHD) or Grade 4 organ toxicity (excluding transaminitis). | Per Grade 2. If improving, manage as appropriate grade above. | Administer methylprednisolone 1000 mg intravenously once per day for 3 days. If improving, manage as appropriate grade above and continue corticosteroids until the severity is Grade 1 or less, then taper as clinically appropriate. If not improving, consider methylprednisolone 1000 mg 2-3 times a day or alternate therapy. [Alternate therapy includes (but is not limited to): anakinra, siltuximab, ruxolitinib, cyclophosphamide, IVIG and ATG.]

Neurologic Toxicity

Monitor patients for signs and symptoms of neurologic toxicity/immune effector cell-associated neurotoxicity syndrome (ICANS) (Table 2). Rule out other causes of neurologic symptoms. Patients who experience Grade 2 or higher neurologic toxicities/ICANS should be monitored with continuous cardiac telemetry and pulse oximetry. Provide intensive-care supportive therapy for severe or life-threatening neurologic toxicities. Consider levetiracetam for seizure prophylaxis for any grade of neurologic toxicities. Physicians may also consider management per current practice guidelines.

Table 2. Neurologic Toxicity/ICANS Grading and Management Guidance
Grading Assessment [Severity based on Common Terminology Criteria for Adverse Events.] | Concurrent CRS | No Concurrent CRS
Grade 1 | Administer tocilizumab per Table 1 for management of Grade 1 CRS. In addition, administer one dose of dexamethasone 10 mg intravenously. If not improving after 2 days, repeat dexamethasone 10 mg intravenously. | Administer one dose of dexamethasone 10 mg intravenously. If not improving after 2 days, repeat dexamethasone 10 mg intravenously.
Grade 1 | Consider levetiracetam for seizure prophylaxis.
Grade 2 | Administer tocilizumab per Table 1 for management of Grade 2 CRS. In addition, administer dexamethasone 10 mg intravenously four times a day. If improving, continue corticosteroids until the severity is Grade 1 or less, then quickly taper as clinically appropriate. If not improving, manage as appropriate grade below. | Administer dexamethasone 10 mg intravenously four times a day. If improving, continue corticosteroids until the severity is Grade 1 or less, then quickly taper as clinically appropriate. If not improving, manage as appropriate grade below.
Grade 2 | Consider levetiracetam for seizure prophylaxis.
Grade 3 | Administer tocilizumab per Table 1 for management of Grade 2 CRS. In addition, administer methylprednisolone 1000 mg intravenously once daily. If improving, manage as appropriate grade above and continue corticosteroids until the severity is Grade 1 or less, then taper as clinically appropriate. If not improving, manage as Grade 4. | Administer methylprednisolone 1000 mg intravenously once daily. If improving, manage as appropriate grade above and continue corticosteroids until the severity is Grade 1 or less, then taper as clinically appropriate. If not improving, manage as Grade 4.
Grade 3 | Consider levetiracetam for seizure prophylaxis.
Grade 4 | Administer tocilizumab per Table 1 for management of Grade 2 CRS. In addition, administer methylprednisolone 1000 mg intravenously twice per day. If improving, manage as appropriate grade above and continue corticosteroids until the severity is Grade 1 or less, then taper as clinically appropriate. If not improving, consider 1000 mg of methylprednisolone intravenously 3 times a day or alternate therapy. [Alternate therapy includes (but is not limited to): anakinra, siltuximab, ruxolitinib, cyclophosphamide, IVIG and ATG.] | Administer methylprednisolone 1000 mg intravenously twice per day. If improving, manage as appropriate grade above and continue corticosteroids until the severity is Grade 1 or less, then taper as clinically appropriate. If not improving, consider 1000 mg of methylprednisolone intravenously 3 times a day or alternate therapy.
Grade 4 | Consider levetiracetam for seizure prophylaxis.

3 DOSAGE FORMS AND STRENGTHS

YESCARTA is available as a cell suspension for infusion.

A single dose of YESCARTA contains 2 × 10^6 CAR-positive viable T cells per kg of body weight (or maximum of 2 × 10^8 CAR-positive viable T cells for patients 100 kg and above) in approximately 68 mL suspension in an infusion bag [see How Supplied/Storage and Handling (16)].

4 CONTRAINDICATIONS

None.

5 WARNINGS AND PRECAUTIONS

5.1 Cytokine Release Syndrome

Cytokine release syndrome (CRS), including fatal or life-threatening reactions, occurred following treatment with YESCARTA. CRS occurred in 90% (379/422) of patients with non-Hodgkin lymphoma (NHL) receiving YESCARTA, including ≥ Grade 3 (Lee grading system^1) CRS in 9%. CRS occurred in 93% (256/276) of patients with large B-cell lymphoma (LBCL), including ≥ Grade 3 CRS in 9% [see Adverse Reactions (6)]. Among patients with LBCL who died after receiving YESCARTA, four had ongoing CRS events at the time of death. For patients with LBCL in Study 2, the median time to onset of CRS was 2 days following infusion (range: 1 to 12 days) and the median duration of CRS was 7 days (range: 2 to 58 days). For patients with LBCL in Study 1, the median time to onset of CRS was 3 days following infusion (range: 1 to 10 days) and the median duration was 7 days (range: 2 to 43 days).

CRS occurred in 84% (123/146) of patients with indolent non-Hodgkin lymphoma (iNHL) in Study 3, including ≥ Grade 3 CRS in 8% [see Adverse Reactions (6)]. Among patients with iNHL who died after receiving YESCARTA, one patient had an ongoing CRS event at the time of death. The median time to onset of CRS was 4 days (range: 1 to 20 days) and the median duration was 6 days (range: 1 to 27 days) for patients with iNHL.

Key manifestations of CRS (≥ 10%) in all patients combined included fever (85%), hypotension (40%), tachycardia (32%), chills (22%), hypoxia (20%), headache (15%), and fatigue (12%). Serious events that may be associated with CRS include cardiac arrhythmias (including atrial fibrillation and ventricular tachycardia), renal insufficiency, cardiac failure, respiratory failure, cardiac arrest, capillary leak syndrome, multi-organ failure, and hemophagocytic lymphohistiocytosis/macrophage activation syndrome (HLH/MAS) [see Adverse Reactions (6)].

The impact of tocilizumab and/or corticosteroids on the incidence and severity of CRS was assessed in two subsequent cohorts of LBCL patients in Study 2. Among patients who received tocilizumab and/or corticosteroids for ongoing Grade 1 events (see Table 1) [see Clinical Trials Experience (6.1)], CRS occurred in 93% (38/41), including 2% (1/41) with Grade 3 CRS; no patients experienced a Grade 4 or 5 event. The median time to onset of CRS was 2 days (range: 1 to 8 days) and the median duration of CRS was 7 days (range: 2 to 16 days).

Prophylactic treatment with corticosteroids was administered to a cohort of 39 patients for 3 days beginning on the day of infusion of YESCARTA [see Clinical Trials Experience (6.1)]. Thirty-one of the 39 patients (79%) developed CRS at which point the patients were managed with tocilizumab and/or therapeutic doses of corticosteroids with no patients developing Grade 3 or higher CRS. The median time to onset of CRS was 5 days (range: 1 to 15 days) and the median duration of CRS was 4 days (range: 1 to 10 days). Although there is no known mechanistic explanation, consider the risk and benefits of prophylactic corticosteroids in the context of pre-existing comorbidities for the individual patient and the potential for the risk of Grade 4 and prolonged neurologic toxicities [See Neurologic Toxicities (5.2)].

Confirm that 2 doses of tocilizumab are available prior to infusion of YESCARTA. Monitor patients at least daily for 7 days following infusion for signs and symptoms of CRS. Monitor patients for signs or symptoms of CRS for 2 weeks after infusion. Counsel patients to seek immediate medical attention should signs or symptoms of CRS occur at any time [see Patient Counseling Information (17)]. At the first sign of CRS, institute treatment with supportive care, tocilizumab, or tocilizumab and corticosteroids as indicated [see Dosage and Administration (2.3)].

5.2 Neurologic Toxicities

Neurologic toxicities (including ICANS) that were fatal or life-threatening occurred following treatment with YESCARTA. Neurologic toxicities occurred in 78% (330/422) of patients with NHL (excluding central nervous system lymphoma) receiving YESCARTA, including ≥ Grade 3 cases in 25% in Study 1, Study 2, and Study 3.

Neurologic toxicities occurred in 87% (94/108) of patients with LBCL in Study 2, including ≥ Grade 3 cases in 31% and in 74% (124/168) of patients in Study 1 including ≥ Grade 3 cases in 25%. The median time to onset was 4 days (range: 1 to 43 days) and the median duration was 17 days in patients with LBCL in Study 2. The median time to onset for neurologic toxicity was 5 days (range:1 to 133 days) and median duration was 15 days in patients with LBCL in Study 1. Neurologic toxicities occurred in 77% (112/146) of patients with iNHL, including ≥ Grade 3 in 21%. The median time to onset was 6 days (range: 1 to 79 days) and the median duration was 16 days. Ninety-eight percent of all neurologic toxicities in patients with LBCL and 99% of all neurologic toxicities in patients with iNHL occurred within the first 8 weeks of YESCARTA infusion. Neurologic toxicities occurred within the first 7 days of YESCARTA infusion in 87% of affected patients with LBCL and 74% of affected patients with iNHL.

The most common neurologic toxicities (≥ 10%) in all patients combined included encephalopathy (50%), headache (43%), tremor (29%), dizziness (21%), aphasia (17%), delirium (15%), and insomnia (10%). Prolonged encephalopathy lasting up to 173 days was noted. Serious events including aphasia, leukoencephalopathy, dysarthria, lethargy, and seizures occurred with YESCARTA. Fatal and serious cases of cerebral edema and encephalopathy, including late-onset encephalopathy, have occurred in patients treated with YESCARTA.

The impact of tocilizumab and/or corticosteroids on the incidence and severity of neurologic toxicities was assessed in two subsequent cohorts of LBCL patients in Study 2. Among patients who received corticosteroids at the onset of Grade 1 toxicities (see Table 2), neurologic toxicities occurred in 78% (32/41) and 20% (8/41) had Grade 3 neurologic toxicities; no patients experienced a Grade 4 or 5 event. The median time to onset of neurologic toxicities was 6 days (range: 1 to 93 days) with a median duration of 8 days (range: 1 to 144 days). Prophylactic treatment with corticosteroids was administered to a cohort of 39 patients for 3 days beginning on the day of infusion of YESCARTA [see Clinical Trials Experience (6.1)]. Of these 39 patients, 85% (33/39) developed neurologic toxicities; 8% (3/39) developed Grade 3 and 5% (2/39) developed Grade 4 neurologic toxicities. The median time to onset of neurological toxicities was 6 days (range: 1 to 274 days) with a median duration of 12 days (range: 1 to 107 days). Prophylactic corticosteroids for management of CRS and neurologic toxicities may result in higher grade of neurologic toxicities or prolongation of neurologic toxicities, delay the onset and decrease the duration of CRS [See Cytokine Release Syndrome (5.1)].

Neurologic toxicities occurred in 85% (11/13) of patients with relapsed or refractory primary central nervous system lymphoma (PCNSL) in Study 4. Thirty-one percent (4/13) of patients had Grade 3 neurologic toxicities. The median time to onset of first neurologic toxicity was 3 days (range: 1 to 9 days) and the median time to onset of first Grade ≥ 3 neurologic toxicity was 9.5 days (range: 5 to 158 days). The median duration of neurologic toxicities was 59 days (range: 52 to 87 days) while 45% (5/11) of patients had ongoing neurological toxicities at the time of study withdrawal, death, or data cut off. The most common neurologic toxicities (≥ 10%) in patients with PCNSL included confusional state (38%), headache (31%), somnolence (31%), disturbance in attention (23%), lethargy (23%), tremor (23%), gait disturbance (15%), hypersomnia (15%), insomnia (15%), and seizures (15%).

Monitor patients at least daily for 7 days following infusion for signs and symptoms of neurologic toxicities. Monitor patients for signs or symptoms of neurologic toxicities for 2 weeks after infusion and treat promptly [see Dosage and Administration (2.3)]. Advise patients to avoid driving for at least 2 weeks following infusion.

5.3 Hypersensitivity Reactions

Allergic reactions may occur with the infusion of YESCARTA. Serious hypersensitivity reactions, including anaphylaxis, may be due to dimethyl sulfoxide (DMSO) or residual gentamicin in YESCARTA.

5.4 Serious Infections

Severe or life-threatening infections occurred in patients after YESCARTA infusion. Infections (all grades) occurred in 45% of patients with NHL. Grade 3 or higher infections occurred in 17% of patients, including Grade 3 or higher infections with an unspecified pathogen in 12%, bacterial infections in 5%, viral infections in 3%, and fungal infections in 1%. YESCARTA should not be administered to patients with clinically significant active systemic infections. Monitor patients for signs and symptoms of infection before and after YESCARTA infusion and treat appropriately. Administer prophylactic antimicrobials according to local guidelines.

Febrile neutropenia was observed in 36% of patients with NHL after YESCARTA infusion and may be concurrent with CRS. In the event of febrile neutropenia, evaluate for infection and manage with broad-spectrum antibiotics, fluids, and other supportive care as medically indicated.

In immunosuppressed patients, including those who have received YESCARTA, life-threatening and fatal opportunistic infections including disseminated fungal infections (e.g., candida sepsis and aspergillus infections) and viral reactivation (e.g., human herpes virus-6 [HHV-6] encephalitis and JC virus progressive multifocal leukoencephalopathy [PML]) have been reported. The possibility of HHV-6 encephalitis and PML should be considered in immunosuppressed patients with neurologic events and appropriate diagnostic evaluations should be performed.

Hepatitis B Virus Reactivation

Hepatitis B virus (HBV) reactivation, in some cases resulting in fulminant hepatitis, hepatic failure, and death, has occurred in patients treated with drugs directed against B cells, including YESCARTA. Perform screening for HBV, HCV, and HIV and management in accordance with clinical guidelines before collection of cells for manufacturing.

5.5 Prolonged Cytopenias

Patients may exhibit cytopenias for several weeks following lymphodepleting chemotherapy and YESCARTA infusion. Grade 3 or higher cytopenias not resolved by Day 30 following YESCARTA infusion occurred in 39% of all patients with NHL and included neutropenia (33%), thrombocytopenia (13%), and anemia (8%). Monitor blood counts after YESCARTA infusion.

5.6 Hypogammaglobulinemia

B-cell aplasia and hypogammaglobulinemia can occur in patients receiving treatment with YESCARTA. Hypogammaglobulinemia was reported as an adverse reaction in 14% of all patients with NHL. Monitor immunoglobulin levels after treatment with YESCARTA and manage using infection precautions, antibiotic prophylaxis, and immunoglobulin replacement.

The safety of immunization with live viral vaccines during or following YESCARTA treatment has not been studied. Vaccination with live virus vaccines is not recommended for at least 6 weeks prior to the start of lymphodepleting chemotherapy, during YESCARTA treatment, and until immune recovery following treatment with YESCARTA.

5.7 Secondary Malignancies

Patients treated with YESCARTA may develop secondary malignancies. T cell malignancies have occurred following treatment of hematologic malignancies with BCMA- and CD19-directed genetically modified autologous T cell immunotherapies, including YESCARTA. Mature T cell malignancies, including CAR-positive tumors, may present as soon as weeks following infusion, and may include fatal outcomes [see Boxed Warning, Adverse Reactions (6.3), Patient Counseling Information (17)].

Monitor life-long for secondary malignancies. In the event that a secondary malignancy occurs, contact Kite at 1-844-454-KITE (5483) to obtain instructions on patient samples to collect for testing.

6 ADVERSE REACTIONS

6.1 Clinical Trials Experience

Because clinical trials are conducted under widely varying conditions, adverse reaction rates observed in the clinical trials of a drug cannot be directly compared to rates in the clinical trials of another drug and may not reflect the rates observed in practice.

The safety data described in the WARNINGS AND PRECAUTIONS and in the ADVERSE REACTIONS sections reflect exposure to a single dose of YESCARTA in four clinical studies, including 168 patients with relapsed or refractory LBCL (Study 1), 108 patients with relapsed or refractory LBCL (Study 2), 146 patients with relapsed or refractory iNHL (including 124 with FL; Study 3), and 13 patients with relapsed or refractory primary CNS lymphoma (PCNSL) (Study 4).

Relapsed or Refractory Large B-cell Lymphoma

Study 1

The safety of YESCARTA was evaluated in Study 1, a randomized, open-label, multicenter study in which patients with primary refractory LBCL or first relapse of LBCL received YESCARTA (N = 168) or standard therapy (N = 168) [see Clinical Studies (14)]. Patients had not yet received treatment for relapsed or refractory lymphoma and were potential candidates for autologous HSCT. The trial excluded patients who were not deemed candidates for transplant or who had a history of central nervous system (CNS) disorders (such as seizures or cerebrovascular ischemia), serious or uncontrolled infection, or autoimmune disease requiring systemic immunosuppression. The study required ANC ≥ 1000/mm^3, platelet count ≥ 75,000/mm^3, creatinine clearance ≥ 60 ml/min, AST/ALT ≤ 2.5 × ULN, and total bilirubin ≤ 1.5 mg/dL.

The median age of the YESCARTA-treated safety population was 59 years (range: 21 to 80 years); 62% were male. The baseline Eastern Cooperative Oncology Group (ECOG) performance status was 0 in 54% of patients and 1 in 46%.

Serious adverse reactions occurred in 50% of patients. The most common serious adverse reactions (> 5%) included CRS, fever, encephalopathy, hypotension, infection with unspecified pathogen, and pneumonia. Fatal adverse reactions occurred in 2% of patients.

Sixty-seven percent (112/168) of patients received tocilizumab after infusion of YESCARTA.

Table 3 summarizes selected non-laboratory adverse reactions in patients treated with YESCARTA, and Table 4 summarizes selected new or worsening Grade 3 or 4 laboratory abnormalities.

Table 3. Adverse Reactions in ≥ 10% of Patients with Relapsed or Refractory LBCL in Study 1
Adverse Reaction | YESCARTA N = 168
Adverse Reaction | Any Grade (%) | Grade 3 or Higher (%)
Blood and Lymphatic System Disorder
Febrile neutropenia | 31 | 31
Cardiac Disorders
Tachycardia [Represents a composite of multiple, related preferred terms.] | 43 | 2
Arrhythmia | 14 | 3
Gastrointestinal Disorders
Diarrhea [Diarrhea includes diarrhea, colitis.] | 42 | 3
Nausea | 40 | 2
Abdominal pain | 20 | 4
Constipation | 20 | 0
Vomiting | 20 | 0
Dry Mouth | 10 | 0
General Disorders and Administration Site Conditions
Fever | 93 | 9
Fatigue | 52 | 7
Chills | 28 | 1
Edema | 23 | 1
Immune System Disorders
Cytokine release syndrome [CRS includes coagulopathy, tachycardia, arrhythmia, cardiac failure, diarrhea, nausea, vomiting, fever, fatigue, chills, edema, decreased appetite, musculoskeletal pain, headache, tremor, dizziness, renal insufficiency, cough, hypoxia, dyspnea, pleural effusion, respiratory failure, rash, hypotension, and hypertension.] | 92 | 7
Hypogammaglobulinemia | 11 | 0
Infections and Infestations
Infections with pathogen unspecified | 25 | 8
Viral infections | 15 | 4
Bacterial infections | 10 | 5
Fungal infections | 10 | 1
Metabolism and Nutrition Disorders
Decreased appetite | 24 | 4
Musculoskeletal and Connective Tissue Disorders
Musculoskeletal pain | 40 | 1
Motor dysfunction [Motor dysfunction includes muscle contractions involuntary, muscle spasms, muscle twitching, muscular weakness.] | 15 | 4
Nervous System Disorders
Encephalopathy [Encephalopathy includes encephalopathy, altered state of consciousness, amnesia, apraxia, bradyphrenia, cognitive disorder, confusional state, depressed level of consciousness, disturbance in attention, dysarthria, dysgraphia, dyspraxia, lethargy, loss of consciousness, memory impairment, mental impairment, mental status changes, metabolic encephalopathy, slow speech, somnolence, toxic encephalopathy.] | 46 | 18
Headache | 41 | 3
Tremor | 25 | 1
Dizziness | 25 | 4
Aphasia | 20 | 7
Neuropathy peripheral | 11 | 2
Psychiatric Disorders
Insomnia | 13 | 0
Delirium [Delirium includes delirium, agitation, delusion, disorientation, hallucination, irritability, restlessness.] | 12 | 4
Renal and Urinary Disorders
Renal insufficiency | 11 | 2
Respiratory, Thoracic and Mediastinal Disorders
Cough | 27 | 1
Hypoxia | 21 | 9
Skin and Subcutaneous Tissue Disorders
Rash | 17 | 1
Vascular Disorders
Hypotension | 47 | 11

Other clinically important adverse reactions that occurred in less than 10% of patients treated with YESCARTA include the following:

- Blood and lymphatic system disorders: Coagulopathy (9%)
- Cardiac disorders: Cardiac failure (1%)
- Eye Disorders: Visual impairment (7%)
- Infections and infestations: Pneumonia (8%), Sepsis (4%)
- Nervous system disorders: Ataxia (6%), seizure (3%), myoclonus (2%), facial paralysis (2%), paresis (2%)
- Respiratory, thoracic and mediastinal disorders: Dyspnea (8%), pleural effusion (6%), respiratory failure (2%)
- Vascular disorders: Hypertension (9%), thrombosis (7%)

Laboratory abnormalities:

Table 4. Grade 3 or 4 Laboratory Abnormalities Occurring in ≥ 10% of Patients with Relapsed or Refractory LBCL in Study 1 [Baseline lab values were assessed prior to lymphodepleting chemotherapy.] (N = 168)
Laboratory Abnormality | YESCARTA
Laboratory Abnormality | Grades 3 or 4 (%)
Leukocyte decrease | 95
Neutrophil decrease | 94
Lymphocyte decrease | 94
Hemoglobin decrease | 40
Platelet decrease | 26
Sodium decrease | 12
Glucose increase | 11

Study 2

The safety of YESCARTA was evaluated in Study 2, a study in which 108 patients with relapsed or refractory LBCL received CD19-positive CAR T cells based on a recommended dose which was weight-based [see Clinical Studies (14)]. Patients with a history of CNS disorders (such as seizures or cerebrovascular ischemia) or autoimmune disease requiring systemic immunosuppression were ineligible. The median age of the study population was 58 years (range: 23 to 76 years); 68% were male. The baseline Eastern Cooperative Oncology Group (ECOG) performance status was 0 in 43% of patients and 1 in 57% of patients.

The most common adverse reactions (incidence ≥ 20%) included CRS, fever, hypotension, encephalopathy, tachycardia, fatigue, headache, decreased appetite, chills, diarrhea, febrile neutropenia, infections with pathogen unspecified, nausea, hypoxia, tremor, cough, vomiting, dizziness, constipation, and cardiac arrhythmias. Serious adverse reactions occurred in 52% of patients. The most common serious adverse reactions (> 2%) included encephalopathy, fever, lung infection, febrile neutropenia, cardiac arrhythmia, cardiac failure, urinary tract infection, renal insufficiency, aphasia, cardiac arrest, Clostridium difficile infection, delirium, hypotension, and hypoxia.

The most common (≥ 10%) Grade 3 or higher reactions included febrile neutropenia, fever, CRS, encephalopathy, infections with pathogen unspecified, hypotension, hypoxia, and lung infections.

Forty-five percent (49/108) of patients received tocilizumab after infusion of YESCARTA.

Table 5 summarizes non-laboratory adverse reactions that occurred in ≥ 10% of patients treated with YESCARTA, and Table 6 describes the laboratory abnormalities of Grade 3 or 4 that occurred in ≥ 10% of patients.

Table 5. Adverse Reactions Observed in ≥ 10% of Patients with Relapsed or Refractory LBCL in Study 2 (N = 108)
Adverse Reaction | Any Grade (%) | Grade 3 or Higher (%)
Blood and Lymphatic System Disorders
Febrile neutropenia | 34 | 31
Cardiac Disorders
Tachycardia [Represents a composite of multiple, related preferred terms.] | 57 | 2
Arrhythmia | 23 | 7
Gastrointestinal Disorders
Diarrhea | 38 | 4
Nausea | 34 | 0
Vomiting | 26 | 1
Constipation | 23 | 0
Abdominal pain | 14 | 1
Dry mouth | 11 | 0
General Disorders and Administration Site Conditions
Fever [Fever includes fever, febrile neutropenia.] | 86 | 16
Fatigue | 46 | 3
Chills | 40 | 0
Edema | 19 | 1
Immune System Disorders
Cytokine release syndrome [CRS includes tachycardia, arrhythmia, fever, chills, hypoxia, renal insufficiency, and hypotension.] | 94 | 13
Hypogammaglobulinemia | 15 | 0
Infections and Infestations
Infections with pathogen unspecified | 26 | 16
Viral infections | 16 | 4
Bacterial infections | 13 | 9
Investigations
Decreased appetite | 44 | 2
Weight decreased | 16 | 0
Dehydration | 11 | 3
Musculoskeletal and Connective Tissue Disorders
Motor dysfunction [Motor dysfunction includes muscle spasms, muscular weakness.] | 19 | 1
Pain in extremity | 17 | 2
Back pain | 15 | 1
Muscle pain | 14 | 1
Arthralgia | 10 | 0
Nervous System Disorders
Encephalopathy [Encephalopathy includes cognitive disorder, confusional state, depressed level of consciousness, disturbance in attention, encephalopathy, hypersomnia, leukoencephalopathy, memory impairment, mental status changes, paranoia, somnolence, stupor.] | 57 | 29
Headache | 45 | 1
Tremor | 31 | 2
Dizziness | 21 | 1
Aphasia | 18 | 6
Psychiatric Disorders
Delirium [Delirium includes agitation, delirium, delusion, disorientation, hallucination, hyperactivity, irritability, restlessness.] | 17 | 6
Respiratory, Thoracic and Mediastinal Disorders
Hypoxia | 32 | 11
Cough | 30 | 0
Dyspnea [Dyspnea includes acute respiratory failure, dyspnea, orthopnea, respiratory distress.] | 19 | 3
Pleural effusion | 13 | 2
Renal and Urinary Disorders
Renal insufficiency | 12 | 5
Vascular Disorders
Hypotension | 57 | 15
Hypertension | 15 | 6
Thrombosis [Thrombosis includes deep vein thrombosis, embolism, embolism venous, pulmonary embolism, splenic infarction, splenic vein thrombosis, subclavian vein thrombosis, thrombosis, thrombosis in device.] | 10 | 1

Other clinically important adverse reactions that occurred in less than 10% of patients treated with YESCARTA include the following:

- Blood and lymphatic system disorders: Coagulopathy (2%)
- Cardiac disorders: Cardiac failure (6%), cardiac arrest (4%)
- Immune system disorders: Hemophagocytic lymphohistiocytosis/macrophage activation syndrome (HLH/MAS) (1%), hypersensitivity (1%)
- Infections and infestations disorders: Fungal infections (5%)
- Nervous system disorders: Ataxia (6%), seizure (4%), dyscalculia (2%), myoclonus (2%)
- Respiratory, thoracic and mediastinal disorders: Pulmonary edema (9%)
- Skin and subcutaneous tissue disorders: Rash (9%)
- Vascular disorders: Capillary leak syndrome (3%)

Laboratory abnormalities:

Table 6. Grade 3 or 4 Laboratory Abnormalities Occurring in ≥ 10% of Patients with Relapsed or Refractory LBCL in Study 2 [Baseline lab values were assessed prior to lymphodepleting chemotherapy.] (N = 108)
Laboratory Abnormality | Grades 3 or 4 (%)
Lymphocyte decrease | 96
Leukocyte decrease | 96
Neutrophil decrease | 92
Hemoglobin decrease | 60
Platelet decrease | 56
Phosphate decrease | 52
Sodium decrease | 19
Albumin decrease | 19
Direct bilirubin increased | 14
Uric acid increased | 13
Potassium decrease | 11

The safety and efficacy of YESCARTA was evaluated in two subsequent cohorts of LBCL patients. The first subsequent, open label, safety management cohort in Study 2 evaluated the safety and efficacy of YESCARTA with the use of tocilizumab and/or corticosteroid and prophylactic levetiracetam (750 mg PO or IV twice daily) for Grade 1 CRS or neurologic events (see Tables 1 and 2). A total of 46 patients with relapsed or refractory LBCL were enrolled and 41 patients were treated with YESCARTA. Of the remaining 5 patients who were not treated, 2 patients died prior to receiving YESCARTA and 3 patients were ineligible due to disease progression. Twenty-eight patients (68%) treated with YESCARTA received bridging therapy between leukapheresis and lymphodepleting chemotherapy. Thirty-two patients (78%) treated with YESCARTA received tocilizumab and/or corticosteroid for CRS and/or neurologic events. Fifteen of 36 with Grade 1 CRS and 21 of 24 patients with Grade 2 CRS received tocilizumab and/or corticosteroids. Among patients who received treatment for Grade 1 or Grade 2 CRS, most patients (13 of 15 and 19 of 21 patients, respectively) received both tocilizumab and corticosteroids. Most patients received 1 or 2 doses of each drug. Ten of 27 patients with Grade 1 and 7 of 15 patients with Grade 2 neurologic events received corticosteroids alone or in combination with tocilizumab.

The second subsequent, open label, safety management cohort in Study 2 evaluated the safety and efficacy of YESCARTA with the use of prophylactic corticosteroids (oral dexamethasone 10 mg once daily for 3 days, starting prior to YESCARTA infusion on Day 0) and prophylactic levetiracetam (750 mg PO or IV) [see Warnings and Precautions (5.1 and 5.2)].

Primary Central Nervous System Lymphoma

Study 4

The safety of YESCARTA was evaluated in a single-arm, single-center, open-label study which included 13 patients with relapsed or refractory PCNSL. Patients with a history or presence of non-malignant CNS disorders or autoimmune disease requiring systemic immunosuppression were ineligible. All patients received lymphodepleting chemotherapy prior to YESCARTA infusion. Four of 13 (31%) patients were receiving corticosteroids at the time of YESCARTA infusion and 12/13 (92%) received a corticosteroid after YESCARTA infusion. Twelve patients (92%) received prophylactic anticonvulsants. The median age was 64 years (range 56 to 68 years), 46% were female, 77% were white, and 15% were Asian.

Table 7 summarizes non-laboratory adverse reactions that occurred in ≥ 10% of patients treated with YESCARTA.

Table 7 Adverse Reactions Observed in ≥10% Patients with Relapsed or Refractory PCNSL in Study 4 (N = 13)
Adverse Reactions | All Grades n (%) | Grade 3 or 4 n (%)
Cardiac Disorders
Sinus tachycardia | 12 (92) | 0 (0)
Arrhythmia [Represents a composite of multiple, related preferred terms.] | 2 (15) | 0 (0)
Eye Disorders
Visual impairment | 2 (15) | 0 (0)
Gastrointestinal Disorders
Diarrhea | 7 (54) | 0 (0)
Vomiting | 7 (54) | 0 (0)
Nausea | 5 (38) | 1 (8)
Constipation | 5 (38) | 0 (0)
Dry mouth | 3 (23) | 0 (0)
General Disorders and Administration Site Conditions
Pyrexia | 11 (85) | 1 (8)
Chills | 7 (54) | 0 (0)
Fatigue | 7 (54) | 0 (0)
Gait disturbance | 4 (31) | 1 (8)
Edema | 3 (23) | 0 (0)
Immune System Disorders
Cytokine Release Syndrome | 11 (85) | 0 (0)
Investigations
Weight decreased | 4 (31) | 0 (0)
Musculoskeletal and Connective Tissue Disorders
Musculoskeletal pain [Musculoskeletal pain also includes Arthralgia.] | 7 (54) | 0 (0)
Muscular weakness | 5 (38) | 1 (8)
Nervous System Disorders
Headache | 11 (85) | 1 (8)
Encephalopathy [Encephalopathy includes Amnesia, Confusional state, Disturbance in attention, Dysarthria, Lethargy, Somnolence.] | 9 (69) | 2 (15)
Dizziness | 5 (38) | 0 (0)
Tremor | 4 (31) | 1 (8)
Hemiparesis | 3 (23) | 0 (0)
Seizure | 2 (15) | 2 (15)
Hypersomnia | 2 (15) | 0 (0)
Psychiatric Disorders
Insomnia | 4 (31) | 0 (0)
Delirium [Delirium includes Agitation, Irritability.] | 3 (23) | 0 (0)
Affective disorder [Affective disorder incudes Anxiety, Depression.] | 2 (15) | 0 (0)
Renal and Urinary Disorders
Acute kidney injury | 2 (15) | 0 (0)
Respiratory, Thoracic and Mediastinal Disorders
Hypoxia | 7 (54) | 1 (8)
Cough | 6 (46) | 0 (0)
Dyspnea | 4 (31) | 0 (0)
Nasal congestion | 3 (23) | 0 (0)
Skin and Subcutaneous Tissue Disorders
Rash maculo-papular | 7 (54) | 0 (0)
Vascular Disorders
Hypotension | 8 (62) | 3 (23)
Thrombosis [Thrombosis includes Deep vein thrombosis, Embolism.] | 5 (38) | 1 (8)

Other clinically important adverse reactions occurred in one patient who had Grade 4 meningitis and ICANS.

Relapsed or Refractory Follicular Lymphoma

Study 3

The safety of YESCARTA was evaluated in Study 3, a study that included 146 patients with relapsed or refractory iNHL (124 patients with FL and 22 with marginal zone lymphoma) who received CD19-positive CAR T cells [see Clinical Studies (14)]. Patients with a history of CNS disorders or autoimmune disease requiring systemic immunosuppression were ineligible. The median age was 61 years (range: 34 to 79 years), 43% were female, 93% were white, 3% were black, and 1% were Asian.

The most common non-laboratory adverse reactions (incidence ≥ 20%) included fever, CRS, hypotension, encephalopathy, fatigue, headache, infections with pathogen unspecified, tachycardia, febrile neutropenia, musculoskeletal pain, nausea, tremor, chills, diarrhea, constipation, decreased appetite, cough, vomiting, hypoxia, arrhythmia, and dizziness. Serious adverse reactions occurred in 48% of patients. Serious adverse reactions in > 2% of patients included febrile neutropenia, encephalopathy, fever, CRS, infections with pathogen unspecified, pneumonia, hypoxia, and hypotension.

The most common (≥ 10%) Grade 3 or higher reactions included febrile neutropenia, encephalopathy, and infections with pathogen unspecified. Fatal adverse reactions occurred in 1% of patients and included CRS and fungal infection.

Fifty-one percent (75/146) of patients received tocilizumab after infusion of YESCARTA.

Table 8 summarizes the adverse reactions, excluding laboratory terms, that occurred in at least 10% of patients treated with YESCARTA and Table 9 describes Grade 3 or 4 laboratory abnormalities that developed or worsened in at least 10% of patients.

Table 8. Adverse Reactions in ≥ 10% of Patients with Relapsed or Refractory FL in Study 3 (N = 146)
Adverse Reaction | Any Grade (%) | Grade 3 or Higher (%)
Blood and lymphatic system disorders
Febrile neutropenia [Represents a composite of multiple, related preferred terms.] | 41 | 41
Cardiac Disorders
Tachycardia | 44 | 1
Arrhythmia | 21 | 2
Gastrointestinal Disorders
Nausea | 40 | 0
Diarrhea [Diarrhea includes diarrhea, colitis, enteritis.] | 29 | 1
Constipation | 28 | 0
Vomiting | 24 | 1
Abdominal pain | 16 | 0
General Disorders and Administration Site Conditions
Fever | 85 | 8
Fatigue | 49 | 1
Chills | 29 | 0
Edema | 13 | 1
Immune System Disorders
Cytokine release syndrome | 84 | 8
Immunoglobulins decreased | 18 | 1
Infections and Infestations
Infections with pathogen unspecified | 45 | 14
Pneumonia | 13 | 8
Fungal infections | 12 | 2
Viral Infections | 13 | 2
Metabolism and Nutrition Disorders
Decreased appetite | 26 | 1
Musculoskeletal and Connective Tissue Disorders
Musculoskeletal pain [Musculoskeletal pain includes musculoskeletal pain, arthralgia, back pain, bone pain, flank pain, groin pain, musculoskeletal chest pain, myalgia, neck pain, osteoarthritis, pain in extremity.] | 40 | 1
Motor dysfunction [Motor dysfunction includes motor dysfunction, muscle rigidity, muscle spasms, muscle strain, muscular weakness.] | 18 | 2
Nervous System Disorders
Encephalopathy [Encephalopathy includes agraphia, amnesia, aphonia, apraxia, CAR T-cell-related encephalopathy syndrome, cognitive disorder, disturbance in attention, dysarthria, dysgraphia, dyskinesia, encephalopathy, lethargy, loss of consciousness, memory impairment, somnolence, speech disorder, confusional state, mental status changes, immune effector cell-associated neurotoxicity, neurotoxicity, toxic encephalopathy.] | 49 | 16
Headache | 45 | 1
Tremor | 31 | 1
Dizziness | 20 | 0
Aphasia | 14 | 4
Neuropathy peripheral | 12 | 0
Ataxia [Ataxia includes ataxia, balance disorder, gait disturbance, vestibular disorder.] | 10 | 0
Psychiatric Disorders
Delirium [Delirium includes agitation, delirium, hallucination, restlessness.] | 16 | 5
Insomnia | 16 | 0
Affective disorder [Affective disorder includes anxiety, depression, impulsive behavior, mania, panic attack.] | 10 | 1
Respiratory, Thoracic and Mediastinal Disorders
Cough | 25 | 0
Hypoxia | 23 | 8
Dyspnea | 12 | 1
Nasal congestion | 10 | 0
Skin and Subcutaneous Tissue Disorders
Rash | 19 | 3
Vascular Disorders
Hypotension | 51 | 4
Hypertension | 13 | 6
Thrombosis [Thrombosis includes deep vein thrombosis, embolism, peripheral ischemia, pulmonary embolism, thrombosis in device, vascular occlusion, jugular vein thrombosis.] | 12 | 4

Other clinically important adverse reactions that occurred in less than 10% of patients treated with YESCARTA include the following:

- Blood and lymphatic system disorders: Coagulopathy (6%)
- Cardiac disorders: Cardiac failure (2%)
- Eye disorders: Visual impairment (5%), blindness (1%)
- Gastrointestinal disorders: Dysphagia (6%)
- General disorders and administration site conditions: Multiple organ dysfunction syndrome (1%)
- Infections and infestations: Bacterial infections (8%), sepsis (2%), herpesvirus infection (4%)
- Musculoskeletal and connective tissue disorders: Muscle injury (1%)
- Nervous system disorders: Seizure (2%), hemiparesis (2%), ischemic stroke (1%)
- Renal and urinary disorders: Renal insufficiency (8%)
- Respiratory, thoracic and mediastinal disorders: Respiratory failure (1%)
- Vascular disorders: Hemorrhage (8%)

Laboratory abnormalities:

Table 9. Grade 3 or 4 Laboratory Abnormalities Occurring in ≥ 10% of Patients with Relapsed or Refractory FL in Study 3 [Baseline lab values were assessed prior to lymphodepleting chemotherapy.] (N = 146)
Laboratory Abnormality | Grades 3 or 4 (%)
Lymphocyte decrease | 96
Leukocyte decrease | 94
Neutrophil decrease | 92
Platelet decrease | 35
Hemoglobin decrease | 32
Phosphate decrease | 25
Sodium decrease | 10
Glucose increase | 10
Calcium decrease | 10

6.2 Postmarketing Experience

Because adverse events to marketed products are reported voluntarily from a population of uncertain size, it is not always possible to reliably estimate their frequency or establish a causal relationship to product exposure.

The following adverse event has been identified during postmarketing use of YESCARTA.

Nervous System Disorders: Spinal cord edema, myelitis, quadriplegia, dysphagia, and status epilepticus.

Immune System Disorders: Infusion related reactions

Neoplasms: T cell malignancies

8 USE IN SPECIFIC POPULATIONS

8.1 Pregnancy

Risk Summary

There are no available data with YESCARTA use in pregnant women. No animal reproductive and developmental toxicity studies have been conducted with YESCARTA to assess whether it can cause fetal harm when administered to a pregnant woman. It is not known if YESCARTA has the potential to be transferred to the fetus. Based on the mechanism of action, if the transduced cells cross the placenta, they may cause fetal toxicity, including B-cell lymphocytopenia. Therefore, YESCARTA is not recommended for women who are pregnant, and pregnancy after YESCARTA infusion should be discussed with the treating physician.

In the U.S. general population, the estimated background risk of major birth defects and miscarriage in clinically recognized pregnancies is 2% – 4% and 15% – 20%, respectively.

8.2 Lactation

Risk Summary

There is no information regarding the presence of YESCARTA in human milk, the effect on the breastfed infant, and the effects on milk production. The developmental and health benefits of breastfeeding should be considered along with the mother's clinical need for YESCARTA and any potential adverse effects on the breastfed infant from YESCARTA or from the underlying maternal condition.

8.3 Females and Males of Reproductive Potential

Pregnancy Testing

Pregnancy status of females with reproductive potential should be verified. Sexually active females of reproductive potential should have a pregnancy test prior to starting treatment with YESCARTA.

Contraception

See the prescribing information for fludarabine and cyclophosphamide for information on the need for effective contraception in patients who receive the lymphodepleting chemotherapy.

There are insufficient exposure data to provide a recommendation concerning duration of contraception following treatment with YESCARTA.

Infertility

There are no data on the effect of YESCARTA on fertility.

8.4 Pediatric Use

The safety and efficacy of YESCARTA have not been established in pediatric patients.

8.5 Geriatric Use

Of the 422 patients with NHL who received YESCARTA in clinical trials, 127 patients (30%) were 65 years of age and older. No clinically important differences in safety or effectiveness were observed between patients aged 65 years and older and younger patients.

11 DESCRIPTION

YESCARTA (axicabtagene ciloleucel) is a CD19-directed genetically modified autologous T cell immunotherapy. To prepare YESCARTA, a patient's own T cells are harvested and genetically modified ex vivo by retroviral transduction to express a chimeric antigen receptor (CAR) comprising a murine anti-CD19 single chain variable fragment (scFv) linked to CD28 and CD3-zeta co-stimulatory domains. The anti-CD19 CAR T cells are expanded and infused back into the patient, where they can recognize and eliminate CD19-expressing target cells.

YESCARTA is prepared from the patient's peripheral blood mononuclear cells, which are obtained via a standard leukapheresis procedure. The mononuclear cells are enriched for T cells and activated with anti-CD3 antibody in the presence of IL-2, then transduced with the replication incompetent retroviral vector containing the anti-CD19 CAR transgene. The transduced T cells are expanded in cell culture, washed, formulated into a suspension, and cryopreserved. The product must pass a sterility test before release for shipping as a frozen suspension in a patient-specific infusion bag. The product is thawed prior to infusion [see Dosage and Administration (2.2), How Supplied/Storage and Handling (16)].

In addition to T cells, YESCARTA may contain NK and NK-T cells. The formulation contains 5% dimethyl sulfoxide (DMSO) and 2.5% albumin (human).

12 CLINICAL PHARMACOLOGY

12.1 Mechanism of Action

YESCARTA, a CD19-directed genetically modified autologous T cell immunotherapy, binds to CD19-expressing cancer cells and normal B cells. Studies demonstrated that following anti-CD19 CAR T cell engagement with CD19-expressing target cells, the CD28 and CD3-zeta co-stimulatory domains activate downstream signaling cascades that lead to T cell activation, proliferation, acquisition of effector functions and secretion of inflammatory cytokines and chemokines. This sequence of events leads to killing of CD19-expressing cells.

12.2 Pharmacodynamics

After YESCARTA infusion, pharmacodynamic responses were evaluated over a 4-week interval by measuring transient elevation of cytokines, chemokines and other molecules in blood. Levels of cytokines and chemokines such as IL-6, IL-8, IL-10, IL-15, TNF-α, IFN-γ, and sIL2Rα were analyzed. Peak elevation was observed within the first 14 days after infusion, and levels generally returned to baseline within 28 days.

Due to the on-target effect of YESCARTA, a period of B-cell aplasia is expected.

Large B-cell lymphoma

Among patients with LBCL with an ongoing response at 24 months in the Study 1 study, 21 of 61 evaluable patients (34%) had no detectable B cells at baseline, and the majority of patients at Month 3 (43 of 69 evaluable patients [62%]) and Month 6 (8 of 13 evaluable patients [62%]) had no detectable B cells. At Month 24, 20 of 24 evaluable patients (83%) had detectable B cells.

Among patients with LBCL with an ongoing response at 24 months in the Study 2 study, 13 of 29 evaluable patients (45%) had no detectable B cells at baseline, and the majority of patients at Month 3 (28 of 35 evaluable patients [80%]) and Month 6 (25 of 32 evaluable patients [78%]) had no detectable B cells. At Month 24, 24 of 32 evaluable patients (75%) had detectable B cells.

12.3 Pharmacokinetics

Following infusion of YESCARTA, anti-CD19 CAR T cells exhibited an initial rapid expansion followed by a decline to near baseline levels by 3 months. Peak levels of anti-CD19 CAR T cells occurred within the first 7 - 14 days after YESCARTA infusion.

Age (range: 21 to 80 years) and gender had no significant impact on AUC Day 0 - 28 and Cmax of YESCARTA.

Large B-cell Lymphoma

Among patients with LBCL in the Study 2 study (n=96 evaluable), the number of anti-CD19 CAR T cells in blood was positively associated with objective response (CR or PR). The median anti-CD19 CAR T cell Cmax levels in responders (n=73) were 205% higher compared to the corresponding level in nonresponders (n=23) (43.6 cells/μL vs 21.2 cells/μL). Median AUC Day 0 - 28 in responding patients (n=73) was 251% of the corresponding level in nonresponders (n=23) (557.1 days × cells/μL vs. 222.0 days × cells/μL).

Among patients with LBCL in the Study 1 study (n=162 evaluable), the number of anti-CD19 CAR T cells in blood was positively associated with objective response [complete remission (CR) or partial remission (PR)]. The median anti-CD19 CAR T cell Cmax levels in responders (n=142) were 275% higher compared to the corresponding level in nonresponders (n=20) (28.9 cells/μL vs 10.5 cells/μL). Median AUC Day 0 - 28 in responding patients (n=142) was 418% of the corresponding level in nonresponders (n=20) (292.9 days × cells/μL vs. 70.1 days × cells/μL). No association between peak anti-CD19 CAR T-cell levels and OS was observed among 163 subjects with an evaluable pharmacokinetic sample when anti-CD19 CAR T-cell peaks were categorized as > median relative to ≤ median.

Follicular Lymphoma

Among patients with FL in the Study 3 study (n=81 evaluable), the median anti-CD19 CAR T cell Cmax levels in responders (n=74) were 40.1 cells/μL and 46.0 cells/μL in nonresponders (n=7). The median AUC Day 0 - 28 in responding FL patients (n=74) were 465.8 days × cells/μL and 404.5 days × cells/μL in nonresponders (n=7).

Some patients required tocilizumab and corticosteroids for management of CRS and neurologic toxicities. Patients treated with tocilizumab (n=44) had 262% and 232% higher anti-CD19 CAR T cells as measured by AUC Day 0 - 28 and Cmax respectively, as compared to patients who did not receive tocilizumab (n=57). Similarly, patients that received corticosteroids (n=26) had 217% and 155% higher AUC Day 0 - 28 and Cmax compared to patients who did not receive corticosteroids (n=75).

Primary Central Nervous System Lymphoma

In Study 4 (n=13), anti-CD19 CAR T cells were measurable in all 13 participants, with a median peak of 75.15 cells/μL (range: 1.97-181.61) at Day 8 and median AUC₀₋₂₈ of 519.98 cells/μL*days (range: 32.36-1549.28).

Hepatic and renal impairment studies of YESCARTA were not conducted.

12.6 Immunogenicity

The observed incidence of anti-drug antibodies is highly dependent on the sensitivity and specificity of the assay. Differences in assay methods preclude meaningful comparisons of the incidence of anti-product antibodies in the studies described below with the incidence of anti-product antibodies in other studies, including those of YESCARTA or of other similar products.

YESCARTA has the potential to induce anti-product antibodies. The immunogenicity of YESCARTA has been evaluated using an enzyme-linked immunosorbent assay (ELISA) for the detection of binding antibodies against FMC63, the originating antibody of the anti-CD19 CAR. Eleven patients (4%) tested positive for pre-dose anti-FMC63 antibodies at baseline in Study 1 and Study 2, and one patient (1%) who had a negative test result at baseline had a positive test result post administration of YESCARTA in the screening ELISA in Study 1. In Study 3, 19 patients (13%) were antibody-positive at baseline, and 3 patients (2%) who had negative test results at baseline had positive test results post administration of YESCARTA in the screening ELISA. Results of a confirmatory cell-based assay, leveraging a properly folded and expressed extracellular portion of the CAR (ScFv, hinge and linker) demonstrated that all patients treated with YESCARTA that had a positive result in the screening ELISA were antibody negative at all time points tested. There is no evidence that the kinetics of initial expansion and persistence of YESCARTA, or the safety or effectiveness of YESCARTA, was altered in these patients.

13 NONCLINICAL TOXICOLOGY

13.1 Carcinogenesis, Mutagenesis, Impairment of Fertility

No carcinogenicity or genotoxicity studies have been conducted with YESCARTA. No studies have been conducted to evaluate the effects of YESCARTA on fertility.

14 CLINICAL STUDIES

14.1 Relapsed or Refractory Large B-Cell Lymphoma

Study 1

A randomized, open-label, multicenter trial evaluated the efficacy of YESCARTA in adult patients with relapsed or refractory LBCL after first-line chemoimmunotherapy that included rituximab and anthracycline (Study 1; NCT03391466). Patients had not yet received treatment for relapsed or refractory lymphoma and were potential candidates for autologous HSCT. Patients were required to have primary refractory disease or relapse within 12 months following completion of first-line therapy. The study excluded patients with primary mediastinal B-cell lymphoma, any history of central nervous system lymphoma, need for urgent therapy due to tumor mass effect, active or serious infections, and ECOG performance status of 2 or greater.

In total, 359 patients were randomized in a 1:1 ratio to receive a single infusion of YESCARTA or to receive second-line standard therapy, consisting of 2 or 3 cycles of chemoimmunotherapy followed by high-dose therapy and autologous HSCT in patients who attained CR or PR. Randomization was stratified by response to first-line therapy and second-line age-adjusted International Prognostic Index.

Following lymphodepleting chemotherapy, YESCARTA was administered as a single intravenous infusion at a target dose of 2 × 10^6 CAR-positive viable T cells/kg (maximum permitted dose: 2 × 10^8 cells). The lymphodepleting regimen consisted of cyclophosphamide 500 mg/m^2 intravenously and fludarabine 30 mg/m^2 intravenously, both given on the fifth, fourth, and third day before YESCARTA. All patients who received YESCARTA were monitored at a healthcare facility for a minimum of 7 days. Bridging therapy, administered between leukapheresis and lymphodepleting chemotherapy, was limited to corticosteroids and was permitted for patients with high disease burden.

In the overall study population, the median age was 59 years (range: 21 to 81 years), 66% were male, 83% were white, 6% were Asian, and 5% were Black. The diagnoses included de novo DLBCL NOS (63%), HGBL with or without MYC and BCL-2 and/or BCL-6 rearrangements (19%), and large cell transformation of follicular lymphoma (13%). In total, 74% of patients had primary refractory LBCL, and 26% had relapsed disease within 12 months of first-line therapy.

Of the 180 patients randomized to receive YESCARTA, 178 underwent leukapheresis and 170 were treated with YESCARTA, of whom 60 (33%) received bridging corticosteroid therapy. Eight patients (4%) were not treated following leukapheresis, primarily due to progressive disease, serious adverse events, or death. The median time from leukapheresis to product delivery was 18 days (range: 13 to 49 days), and from leukapheresis to YESCARTA infusion was 26 days (range: 16 to 52 days). The median dose was 2.0 × 10^6 CAR-positive viable T cells/kg (range: 1.0 to 2.1 × 10^6 cells/kg).

Of the 179 patients randomized to receive standard therapy, 168 patients received any study treatment, and 62 (35%) received high-dose therapy and on-protocol HSCT. The most common reason for not receiving HSCT was lack of response to salvage chemotherapy.

The primary efficacy measure was event-free survival (EFS) as determined by an independent review committee. Efficacy is summarized in Table 9 and Figure 1. With an estimated median follow-up of 22.1 months overall, the estimated EFS rate at 18 months was 41.5% [95% CI: 34.2, 48.6] in the YESCARTA arm and 17.0% [95% CI: 11.8, 23.0] in the standard therapy arm.

In the YESCARTA arm, the estimated median DOR was 28.4 months (95% CI: 26.9, NE) in patients who achieved CR and 1.6 months (95% CI: 1.4, 1.9) in patients who achieved a best response of PR.

At the time of the primary EFS analysis, the interim analysis of overall survival (OS) did not meet criteria for statistical significance. With an estimated median follow-up of 46.7 months overall, the primary analysis of OS showed a statistically significant improvement in the YESCARTA arm compared to the standard therapy arm. Fifty-seven percent of patients received cellular immunotherapy after no response to or relapse after randomization to standard therapy arm.

The efficacy results are summarized in Table 10 and Figure 1 and Figure 2.

Table 10. Efficacy Results for Study 1
Outcome [Per the International Working Group Lugano Classification (Cheson 2014), as assessed by the independent review committee.] | YESCARTA (N = 180) [Two recipients of non-conformal product are included in the efficacy analysis.] | Standard Therapy (N = 179)
Event-Free Survival [EFS is defined as time from randomization to the earliest date of disease progression or relapse, best response of stable disease up to and including the Day 150 assessment, commencement of new lymphoma therapy, or death from any cause.]
Number of events, n (%) | 108 (60) | 144 (80)
Median, months [95% CI] [Kaplan-Meier estimate.] | 8.3 [4.5, 15.8] | 2.0 [1.6, 2.8]
Stratified hazard ratio [95% CI] | 0.40 [0.31, 0.51]
Stratified log-rank p-value | <0.0001
Overall Survival [Overall survival was conducted at the time of the primary OS analysis.]
Number of events, n (%) | 82 (46) | 95 (53)
Median OS, months [95% CI] | NE (28.6, NE) | 31.1 (17.1, NE)
Stratified hazard ratio [95% CI] | 0.73 (0.54, 0.98)
Stratified log-rank p-value [p-value is compared with 0.0249, the one-sided efficacy boundary (significance level) for the primary OS analysis.] | 0.0168
Best Objective Response Rate, % [95% CI] | 83 [77, 88] | 50 [43, 58]
Difference in ORR, % [95% CI] | 33 [23, 42]
Stratified p-value [Per Cochran-Mantel-Haenszel method. For all stratified analyses, stratification was based on response to first-line therapy (primary refractory, vs relapse within 6 months of first-line therapy vs relapse within > 6 but ≤ 12 months) and second-line age-adjusted International Prognostic Index.] | <0.0001
Complete remission rate, % [95% CI] | 65 [58, 72] | 32 [26, 40]
Partial remission rate, % [95% CI] | 18 [13, 25] | 18 [13, 24]
Progression-Free Survival
Number of events, n (%) | 93 (52) | 81 (45)
Median, months [95% CI] | 14.9 [7.2, NE] | 5.0 [3.4, 8.5]
Stratified hazard ratio [95% CI] | 0.56 [0.41, 0.76]
CI, confidence interval; NE, not estimable.

Figure 1. Kaplan-Meier Curve of Event-Free Survival in Study 1 (Primary EFS Analysis)

Figure 2. Kaplan-Meier Curve of Overall Survival in Study 1 (Primary OS Analysis)

Study 2

A single-arm, open-label, multicenter trial evaluated the efficacy of a single infusion of YESCARTA in adult patients with relapsed or refractory aggressive B-cell non-Hodgkin lymphoma (Study 2; NCT02348216). Eligible patients had refractory disease to the most recent therapy or relapse within 1 year after autologous hematopoietic stem cell transplantation (HSCT). The study excluded patients with prior allogeneic HSCT, any history of central nervous system lymphoma, ECOG performance status of 2 or greater, absolute lymphocyte count less than 100/µL, creatinine clearance less than 60 mL/min, hepatic transaminases more than 2.5 times the upper limit of normal, cardiac ejection fraction less than 50%, or active serious infection.

Following lymphodepleting chemotherapy, YESCARTA was administered as a single intravenous infusion at a target dose of 2 × 10^6 CAR-positive viable T cells/kg (maximum permitted dose: 2 × 10^8 cells). The lymphodepleting regimen consisted of cyclophosphamide 500 mg/m^2 intravenously and fludarabine 30 mg/m^2 intravenously, both given on the fifth, fourth, and third day before YESCARTA. Bridging chemotherapy between leukapheresis and lymphodepleting chemotherapy was not permitted. All patients were hospitalized for YESCARTA infusion and for a minimum of 7 days afterward.

Of 111 patients who underwent leukapheresis, 101 received YESCARTA. Of the patients treated, the median age was 58 years (range: 23 to 76 years), 67% were male, and 89% were white. Most (76%) had DLBCL, 16% had transformed follicular lymphoma, and 8% had primary mediastinal large B-cell lymphoma. The median number of prior therapies was 3 (range: 1 to 10), 77% of the patients had refractory disease to a second or greater line of therapy, and 21% had relapsed within 1 year of autologous HSCT.

One out of 111 patients did not receive the product due to manufacturing failure. Nine other patients were not treated, primarily due to progressive disease or serious adverse reactions following leukapheresis. The median time from leukapheresis to product delivery was 17 days (range: 14 to 51 days), and the median time from leukapheresis to infusion was 24 days (range: 16 to 73 days). The median dose was 2.0 × 10^6 CAR-positive viable T cells/kg (range: 1.1 to 2.2 × 10^6 cells/kg).

Efficacy was established on the basis of complete remission (CR) rate and duration of response (DOR), as determined by an independent review committee (Table 11 and Table 12). The median time to response was 0.9 months (range: 0.8 to 6.2 months). Response durations were longer in patients who achieved CR, as compared to patients with a best response of partial remission (PR) (Table 11). Of the 52 patients who achieved CR, 14 initially had stable disease (7 patients) or PR (7 patients), with a median time to improvement of 2.1 months (range: 1.6 to 5.3 months).

Table 11. Response Rate in Patients with Relapsed or Refractory LBCL in Study 2
 | Recipients of YESCARTA (N = 101)
Objective Response Rate [Per 2007 revised International Working Group criteria, as assessed by the independent review committee.] (95% CI) | 73 (72%) (62, 81)
Complete Remission Rate (95% CI) | 52 (51%) (41, 62)
Partial Remission Rate (95% CI) | 21 (21%) (13, 30)
CI, confidence interval.

Table 12. Duration of Response in Patients with Relapsed or Refractory LBCL in Study 2
 | From N of 101
Number of Responders | 73
DOR (Months) [Among all responders. DOR is measured from the date of first objective response to the date of progression or death from relapse or toxicity.]
Median [Kaplan-Meier estimate.] (95% CI) | 9.2 (5.4, NE)
Range [A "+" sign indicates a censored value.] | 0.03+, 14.4+
DOR if Best Response is CR (Months)
Median (95% CI) | NE (8.1, NE)
Range | 0.4, 14.4+
DOR if Best Response is PR (Months)
Median (95% CI) | 2.1 (1.3, 5.3)
Range | 0.03+, 8.4+
Median Follow-up for DOR (Months), | 7.9
CR, complete remission; DOR, duration of response; NE, not estimable; PR, partial remission.

14.2 Relapsed or Refractory Follicular Lymphoma

Study 3

Efficacy in FL is based on a single-arm, open-label, multicenter trial (Study 3; NCT03105336) that evaluated a single infusion of YESCARTA in adult patients with relapsed or refractory FL after two or more lines of systemic therapy, including the combination of an anti-CD20 monoclonal antibody and an alkylating agent. The study excluded patients with active or serious infections, transformed lymphoma or other aggressive lymphomas, prior allogeneic HSCT, or any history of CNS lymphoma or CNS disorders. Following lymphodepleting chemotherapy, YESCARTA was administered as a single intravenous infusion with a target dose of 2 × 10^6 anti-CD19 CAR T cells/kg (maximum permitted dose: 2 × 10^8 cells). The lymphodepleting regimen consisted of cyclophosphamide 500 mg/m^2 intravenously and fludarabine 30 mg/m^2 intravenously, both given on the fifth, fourth, and third day before YESCARTA.

Of 123 patients with FL who underwent leukapheresis, 120 received YESCARTA. Of the remaining three patients (2%) who were not treated, one was ineligible due to thrombocytopenia, one went into remission prior to initiating lymphodepletion, and one died of cardiac arrest. There were no manufacturing failures. Of the 120 patients with FL infused with YESCARTA, the 81 consecutive patients included in the primary efficacy analysis had at least 9 months of potential follow-up from date of first response.

Among the 81 patients with FL included in the primary efficacy analysis, the median age was 62 years (range: 34 to 79 years), 46% were female, 93% were white, 4% were black, and 3% were Asian. The median number of prior systemic therapies was 3 (range: 2 to 9), with 32% having 2 prior lines, 22% having 3 prior lines, and 46% having ≥ 4 prior lines. Thirty-one percent had received a PI3K inhibitor, 72% had progression within 6 months of the most recent regimen, and 56% had progression within 24 months of initiating their first anti-CD20 combination therapy. Between leukapheresis and administration of YESCARTA, one patient (1%) in the primary efficacy analysis received bridging therapy.

Among the 81 patients included in the primary efficacy analysis, the median time from leukapheresis to product delivery was 17 days (range: 13 to 33 days) and leukapheresis to product infusion was 27 days (range: 19 to 250 days). The median dose of YESCARTA was 2.0 × 10^6 CAR T cells/kg (range 1.3 to 2.1 × 10^6 CAR T cells/kg). All treated patients received YESCARTA infusion on day 0 and were hospitalized until at least day 7.

Efficacy was established on the basis of objective response rate and DOR as determined by an independent review committee (Table 13 and Table 14). The median time to response in the primary efficacy population was 1.0 month (range: 0.8 to 3.1 months).

Table 13. Response Rate in Patients with Relapsed or Refractory FL in Study 3
 | Primary Efficacy Analysis (N = 81) | All Leukapheresed Patients (N = 123)
Objective Response Rate [Per the International Working Group Lugano Classification (Cheson 2014), as assessed by the independent review committee.] , n (95% CI) | 74 (91%) (83, 96) | 110 (89%) (83, 94)
Complete Remission [Complete remission required documentation of a negative bone marrow biopsy after treatment, in patients who did not have a negative bone marrow biopsy between their most recent disease progression prior to Study 3 and initiation of lymphodepleting chemotherapy.] , n (95% CI) | 49 (60%) (49, 71) | 76 (62%) (53, 70)
Partial Remission, n (95% CI) | 25 (31%) (21, 42) | 34 (28%) (20, 36)
CI, confidence interval.

Table 14. Duration of Response in Patients with Relapsed or Refractory FL in Study 3
 | From N of 81
Number of Responders | 74
DOR (Months) [Among all responders in the primary efficacy population. DOR is measured from the date of first objective response to the date of progression or death from any cause.]
Median [Kaplan-Meier estimate.] (95% CI) | NE (20.8, NE)
Range [A "+" sign indicates a censored value.] | 0.0, 25.0+
Rate of Continued Remission, , [Measured from the date of first objective response to the date of progression or death.]
At 12 months (95% CI), % | 76.2 (63.9, 84.7)
At 18 months (95% CI), % | 74.2 (61.5, 83.2)
Median Follow-up for DOR (Months), | 14.5
CR, complete remission; DOR, duration of response; NE, not estimable; PR, partial remission.

15 REFERENCES

1. Lee DW et al (2014). Current concepts in the diagnosis and management of cytokine release syndrome. Blood. 2014 Jul 10; 124(2): 188–195.

16 HOW SUPPLIED/STORAGE AND HANDLING

YESCARTA is supplied in an infusion bag (NDC 71287-119-01) containing approximately 68 mL of frozen suspension of genetically modified autologous T cells in 5% DMSO and 2.5% albumin (human).

STORAGE AND HANDLING

Each YESCARTA infusion bag is individually packed in a metal cassette (NDC 71287-119-02). YESCARTA is supplied in a liquid nitrogen dry shipper.

- Match the identity of the patient with the patient identifiers on the cassette and infusion bag upon receipt.
- Store YESCARTA frozen in the vapor phase of liquid nitrogen (less than or equal to -150ºC). YESCARTA may be stored for a single time at -80°C (+/- 10°C), for up to 90 days, and not exceeding the labeled expiration date. Do not return YESCARTA to storage in the vapor phase of liquid nitrogen after storage at -80°C.
- Thaw before using [see Dosage and Administration (2)].

17 PATIENT COUNSELING INFORMATION

Advise the patient to read the FDA-approved patient labeling (Medication Guide).

Ensure that patients understand the risk of manufacturing failure (< 1% in clinical trials). In case of a manufacturing failure, a second manufacturing of YESCARTA may be attempted. In addition, while the patient awaits the product, additional chemotherapy (not the lymphodepletion) may be necessary and may increase the risk of adverse events during the pre-infusion period.

Advise patients to seek immediate attention for any of the following:

- Cytokine Release Syndrome (CRS) - Signs or symptoms associated with CRS, including fever, chills, fatigue, tachycardia, nausea, hypoxia, and hypotension [see Warnings and Precautions (5.1) and Adverse Reactions (6)].
- Neurologic Toxicities - Signs or symptoms associated with neurologic events, including encephalopathy, seizures, changes in level of consciousness, speech disorders, tremors, and confusion [see Warnings and Precautions (5.2) and Adverse Reactions (6)].
- Serious Infections - Signs or symptoms associated with infection [see Warnings and Precautions (5.4) and Adverse Reactions (6)].
- Prolonged Cytopenia - Signs or symptoms associated with bone marrow suppression, including neutropenia, anemia, thrombocytopenia, or febrile neutropenia [see Warnings and Precautions (5.5) and Adverse Reactions (6)].
- Secondary Malignancies - Secondary malignancies, including T cell malignancies, have occurred [see Boxed Warning, Warnings and Precautions (5.7), and Adverse Reactions (6.3)].

Advise patients of the need to:

- Avoid driving for at least 2 weeks.
- Have periodic monitoring of blood counts.
- Contact Kite at 1-844-454-KITE (5483) if they are diagnosed with a secondary malignancy [see Warnings and Precautions (5.7)].

Manufactured by, Packed by, Distributed by:
Kite Pharma, Inc.
Santa Monica, CA 90404
US License No 2064

YESCARTA is a trademark of Kite Pharma, Inc. All other trademarks referenced herein are the property of their respective owners.

© 2026 Kite Pharma, Inc. All Rights Reserved.

125643-GS-016

MEDICATION GUIDE
YESCARTA (pronounced yes-kar-ta)
(axicabtagene ciloleucel)

Read this Medication Guide before you start your YESCARTA treatment. The more you know about your treatment, the more active you can be in your care. Talk with your healthcare provider if you have questions about your health condition or treatment. Reading this Medication Guide does not take the place of talking with your healthcare provider about your treatment.

What is the most important information I should know about YESCARTA?
YESCARTA may cause side effects that are life-threatening and can lead to death. Call or see your healthcare provider or get emergency help right away if you get any of the following:

- Fever (100.4°F/38°C or higher)
- Difficulty breathing
- Chills or shaking chills
- Confusion
- Dizziness or lightheadedness
- Severe nausea, vomiting, or diarrhea
- Fast or irregular heartbeat
- Severe fatigue or weakness

It is important to tell your healthcare provider that you received YESCARTA. Your healthcare provider may give you other medicines to treat your side effects.

What is YESCARTA?
YESCARTA is a prescription medicine used to treat two types of non-Hodgkin lymphoma:

- large B-cell lymphoma when your first treatment did not work or your cancer returned within a year of first treatment, OR when at least two kinds of treatment have failed to control your cancer.
- follicular lymphoma when at least two kinds of treatment have failed to control your cancer.

YESCARTA is different than other cancer medicines because it is made from your own white blood cells, which have been modified to recognize and attack your lymphoma cells.

Before getting YESCARTA, tell your healthcare provider about all your medical problems, including if you have or have had:

- Neurologic problems (such as seizures, stroke, or memory loss)
- Lung or breathing problems
- Heart problems
- Liver problems
- Kidney problems
- A recent or active infection

Tell your healthcare provider about all the medications you take, including prescription and over-the-counter medicines, vitamins, and herbal supplements.

How will I receive YESCARTA?

- Since YESCARTA is made from your own white blood cells, your blood will be collected by a process called "leukapheresis" (loo-kah-fur-ee-sis), which will concentrate your white blood cells.
- Your blood cells will be sent to a manufacturing center to make your YESCARTA.
- Before you get YESCARTA, you will get 3 days of chemotherapy to prepare your body.
- When your YESCARTA is ready, your healthcare provider will give it to you through a catheter placed into your vein (intravenous infusion). The infusion usually takes less than 30 minutes.
- You will be monitored daily for at least 7 days after the infusion.
- You should plan to stay close to a healthcare facility for at least 2 weeks after getting YESCARTA. Your healthcare provider will help you with any side effects that may occur.
- You may be hospitalized for side effects and your healthcare provider will discharge you if your side effects are under control, and it is safe for you to leave the hospital.
- Your healthcare provider will want to do blood tests to follow your progress. It is important that you do have your blood tested. If you miss an appointment, call your healthcare provider as soon as possible to reschedule.

What should I avoid after receiving YESCARTA?

- Avoid driving for at least 2 weeks after you get YESCARTA.
- Do not donate blood, organs, tissues, or cells for transplantation.

What are the possible or reasonably likely side effects of YESCARTA?
The most common side effects of YESCARTA include:

- Fever (100.4°F/38°C or higher)
- Low white blood cells (can occur with a fever)
- Low red blood cells
- Low blood pressure (dizziness or lightheadedness, headache, feeling tired, short of breath)
- Fast heartbeat
- Confusion
- Difficulty speaking or slurred speech
- Nausea
- Diarrhea

YESCARTA may increase your risk of getting cancers including certain types of blood cancers. Your healthcare provider should monitor you for this.
These are not all the possible side effects of YESCARTA. Call your healthcare provider about any side effects that concern you. You may report side effects to the FDA at 1-800-FDA-1088.

General information about the safe and effective use of YESCARTA
Medicines are sometimes prescribed for purposes other than those listed in a Medication Guide. If you would like more information about YESCARTA, talk with your healthcare provider. You can ask your healthcare provider for information about YESCARTA that is written for health professionals. You can get additional information by contacting Kite at 1-844-454-KITE (5483) or at www.Yescarta.com.

What are the ingredients in YESCARTA?
Active ingredients: axicabtagene ciloleucel.
Inactive ingredients: albumin (human); DMSO.
YESCARTA is a trademark of Kite Pharma, Inc. All other trademarks referenced herein are the property of their respective owners.
© 2026 Kite Pharma, Inc. All Rights Reserved.

This Medication Guide has been approved by the U.S. Food and Drug Administration.

Revised: February 2026

Principal Display Panel - Patient ID Label

VERIFY
PATIENT ID

axicabtagene ciloleucel
YESCARTA®

Lot: 123456789-0X

Kite Patient ID: 123456789

Expiration Date: 31-Dec-2900

First Name M.I.: FIRST NAME W

Last Name: LAST NAME

DOB: 31-Dec-1900

Hospital Patient ID: 1234567890123456

DIN:

AS-00827
W0123 45 678900
00
9

Package/Label Principal Display Panel

axicabtagene ciloleucel

YESCARTA

STOP

Confirm patient ID prior to infusion

VERIFY PATIENT ID

Lot: 123456789-0X

Kite Patient ID: 123456789

Expiration Date: 31-Dec-2900

First Name M.I.: FIRST NAME W

Last Name: LAST NAME

DOB.: 31-Dec-1900

Hospital Patient ID: 1234567890123456

DIN:

AS-00829 W0123 45 678900

Principal Display Panel - Lot Label

axicabtagene ciloleucel
YESCARTA®

Kite Pharma, Inc.
Site: FXX

Cell Order: 123456789

LOT: 123456789-01

2400 Broadway, Santa Monica, CA 90404
XXX-XXX-XXXX

AS-00831

Principal Display Panel - 68 mL Bag Cassette Label

NDC 71287-119-02

axicabtagene ciloleucel
YESCARTA®

RX ONLY

FOR AUTOLOGOUS & INTRAVENOUS USE ONLY
No U.S. standard of potency

Dose: One sterile bag for infusion.

Contents: Maximum of 2 x 10^8 autologous anti-CD19 CAR T cells in
approximately 68 mL suspension containing 5% DMSO USP.

Gently mix the contents of
the bag while thawing

See package insert for full
prescribing information and
instructions for administration

Ship and store in vapor phase of
liquid nitrogen ≤ -150°C. Optional
one time storage at -80°C as
indicated in the package insert.

DO NOT USE A
LEUKODEPLETING FILTER

DO NOT IRRADIATE

Manufactured with gentamicin

Not evaluated for infectious
substances

Preservative free

Manufacturer: Kite Pharma, Inc., 2400 Broadway, Santa Monica, CA 90404
Phone: 1-844-454-KITE U.S. Lic. #2064

Kite
A GILEAD Company

MK-00375

Principal Display Panel - 68 mL Bag Label

NDC 71287-119-01

axicabtagene ciloleucel
YESCARTA®

RX ONLY

FOR AUTOLOGOUS & INTRAVENOUS USE ONLY
No U.S. standard of potency

Dose: One sterile bag for infusion.

Contents: Maximum of 2 x 10^8 autologous anti-CD19 CAR T cells in
approximately 68 mL suspension containing 5% DMSO USP.

Gently mix the contents of the bag
while thawing

See package insert for full prescribing
information and instructions for
administration

Ship and store in vapor phase of liquid
nitrogen ≤ -150°C. Optional one time
storage at -80°C as indicated in the
package insert.

DO NOT USE A
LEUKODEPLETING FILTER

DO NOT IRRADIATE

Manufactured with gentamicin

Not evaluated for infectious
substances

Preservative free

Manufacturer: Kite Pharma, Inc., 2400 Broadway, Santa Monica, CA 90404
Phone: 1-844-454-KITE U.S. Lic. #2064

MK-00378